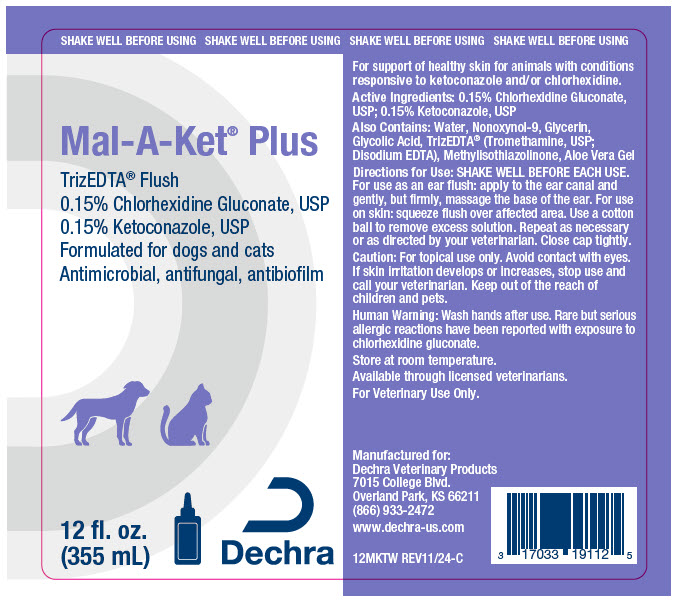 DRUG LABEL: Mal-A-Ket Plus TrizEDTA Flush
NDC: 17033-193 | Form: SOLUTION
Manufacturer: Dechra Veterinary Products, LLC
Category: animal | Type: OTC ANIMAL DRUG LABEL
Date: 20241212

ACTIVE INGREDIENTS: Chlorhexidine Gluconate 1.5 mg/1 mL; Ketoconazole 1.5 mg/1 mL

Mal-A-Ket® Plus TrizEDTA® Flush

VETERINARY INDICATIONS

For support of healthy skin for animals with conditions responsive to ketoconazole and/or chlorhexidine.

DESCRIPTION

Active Ingredients: 0.15% Chlorhexidine Gluconate, USP; 0.15% Ketoconazole, USP

Also Contains: Water, Nonoxynol-9, Glycerin, Glycolic Acid, TrizEDTA® (Tromethamine, USP; Disodium EDTA), Methylisothiazolinone, Aloe Vera Gel

DOSAGE AND ADMINISTRATION

Directions for Use: SHAKE WELL BEFORE EACH USE. For use as an ear flush: apply to the ear canal and gently, but firmly, massage the base of the ear. For use on skin: squeeze flush over affected area. Use a cotton ball to remove excess solution. Repeat as necessary or as directed by your veterinarian. Close cap tightly.

SAFE HANDLING WARNING

Caution: For topical use only. Avoid contact with eyes. If skin irritation develops or increases, stop use and call your veterinarian. Keep out of the reach of children and pets.

WARNINGS

Human Warning: Wash hands after use. Rare but serious allergic reactions have been reported with exposure to chlorhexidine gluconate.

STORAGE AND HANDLING

Store at room temperature.

Available through licensed veterinarians.

For Veterinary Use Only.

Manufactured for:
Dechra Veterinary Products
7015 College Blvd.
Overland Park, KS 66211
(866) 933-2472
www.dechra-us.com

12MKTW REV11/24-C

PRINCIPAL DISPLAY PANEL - 355 mL Bottle Label

SHAKE WELL BEFORE USING

Mal-A-Ket® Plus

TrizEDTA® Flush
0.15% Chlorhexidine Gluconate, USP
0.15% Ketoconazole, USP
Formulated for dogs and cats
Antimicrobial, antifungal, antibiofilm

12 fl. oz.
(355 mL)
Dechra